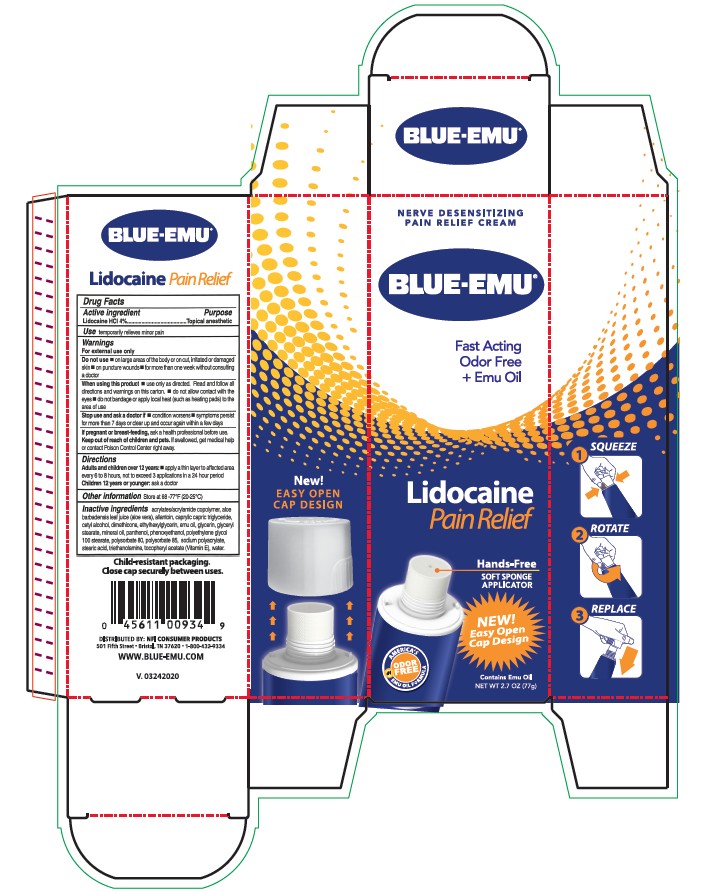 DRUG LABEL: Blue-Emu Lidocaine Pain Relief Cream
NDC: 69993-350 | Form: CREAM
Manufacturer: Kingsway Pharmaceuticals dba NFI, LLC
Category: otc | Type: HUMAN OTC DRUG LABEL
Date: 20250909

ACTIVE INGREDIENTS: LIDOCAINE HYDROCHLORIDE 40 mg/1 1
INACTIVE INGREDIENTS: ALOE VERA LEAF; ALLANTOIN; MEDIUM-CHAIN TRIGLYCERIDES; CETYL ALCOHOL; DIMETHICONE, UNSPECIFIED; ETHYLHEXYLGLYCERIN; EMU OIL; GLYCERIN; GLYCERYL MONOSTEARATE; MINERAL OIL; PANTHENOL; PHENOXYETHANOL; PEG-100 MONOSTEARATE; POLYSORBATE 80; POLYSORBATE 85; SODIUM POLYACRYLATE (8000 MW); STEARIC ACID; TROLAMINE; .ALPHA.-TOCOPHEROL ACETATE; WATER

Blue-Emu® Lidocaine Pain Relief Cream

Active ingredient

Lidocaine HCl 4%

Purpose

Topical anesthetic

Use

temporarily relieves minor pain

Warnings

For external use only

Do not use

- on large areas of the body or on cut, irritated or damaged skin
- on puncture wounds
- for more than one week without consulting a doctor

When using this product

- use only as directed. Read and follow all directions and warnings on this carton.
- do not allow contact with the eyes
- do not bandage or apply local heat (such as heating pads) to the area of use

Stop use and ask a doctor if

- condition worsens
- symptoms persist for more than 7 days or clear up and occur again within a few days

PREGNANCY OR BREAST FEEDING

If pregnant or breast-feeding, ask a health professional before use.

Keep out of reach of children and pets. If swallowed, get medical help or contact Poison Control Center right away.

Directions

Adults and children over 12 years:

- apply a thin layer to affected area every 6 to 8 hours, not to exceed 3 applications in a 24 hour period

Children 12 years or younger: ask a doctor

Other information

Store at 68-77oF (20-25oC)

Inactive ingredients

acrylates/acrylamide copolymer, aloe barbadensis leaf juice (aloe vera), allantoin, caprylic capric triglyceride, cetyl alcohol, dimethicone, ethylhexylglycerin, emu oil, glycerin, glyceryl stearate, mineral oil, panthenol, phenoxyethanol, polyethylene glycol 100 stearate, polysorbate 80, polysorbate 85, sodium polyacrylate, stearic acid, triethanolamine, tocopherol acetate (Vitamin E), water.

Child-resistant packaging.
Close cap securely between uses.
DISTRIBUTED BY: NFI CONSUMER PRODUCTS
501 Fifth Street • Bristol, TN 37620 • 1-800-432-9334
WWW.BLUE-EMU.COM

Principal Display Panel – Carton Label

NERVE DESENSITIZING
PAIN RELIEF CREAM
BLUE-EMU®
Fast Acting
Odor Free
+ Emu Oil
Lidocaine
Pain Relief
Hands-Free
SOFT SPONGE
APPLICATOR
NEW!
Easy Open
Cap Design
AMERICA'S
#1
EMU OIL FORMULA
ODOR
FREE
Contains Emu Oil
NET WT 2.7 OZ (77g)